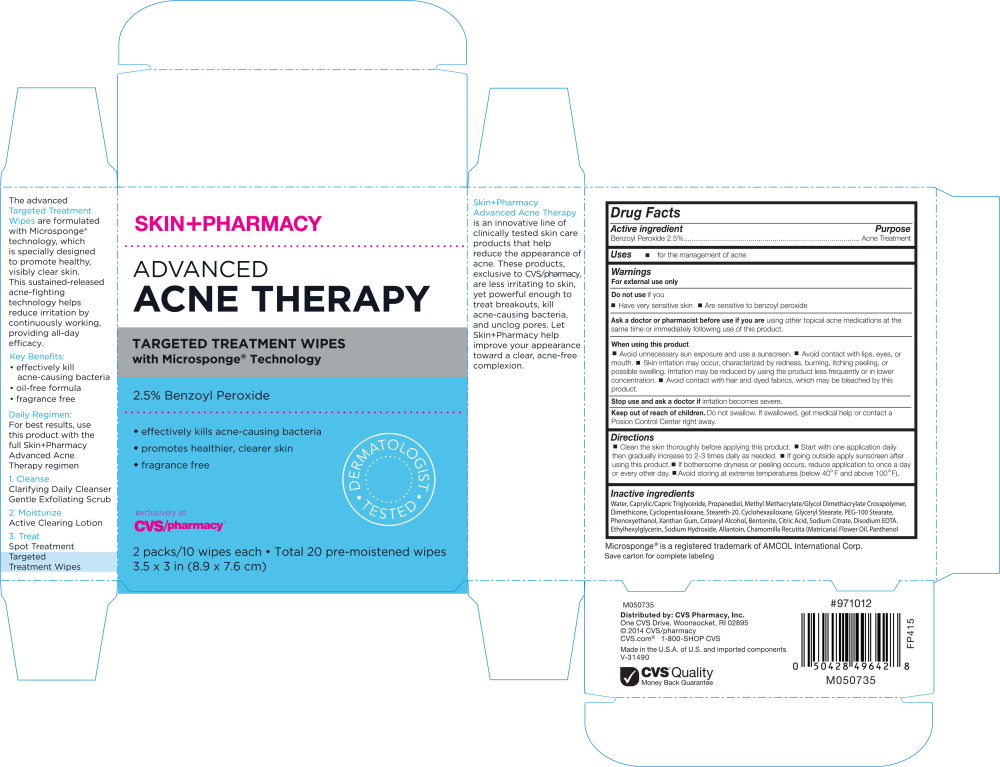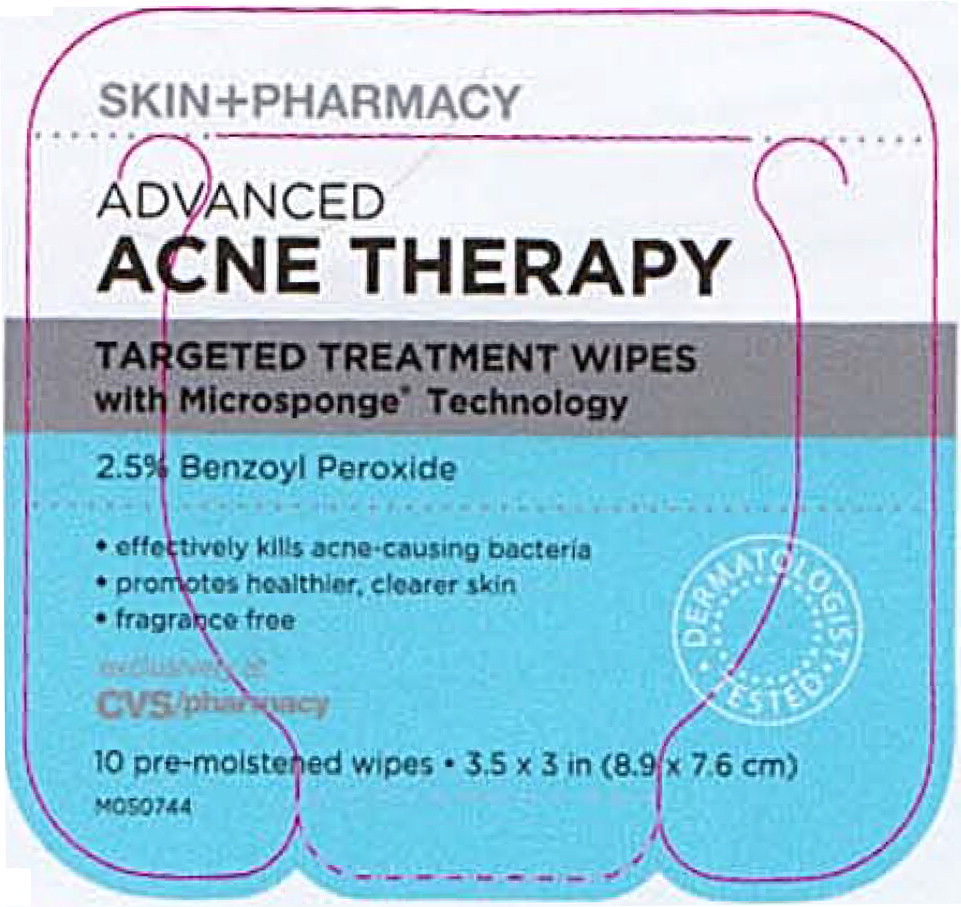 DRUG LABEL: SkinPharmacy Advanced Acne Therapy 
NDC: 69842-081 | Form: SWAB
Manufacturer: CVS Health
Category: otc | Type: HUMAN OTC DRUG LABEL
Date: 20170314

ACTIVE INGREDIENTS: benzoyl peroxide 25 mg/1 mL
INACTIVE INGREDIENTS: water; medium-chain triglycerides; propanediol; methyl methacrylate/glycol dimethacrylate crosspolymer; dimethicone; cyclomethicone 5; steareth-20; cyclomethicone 6; glyceryl monostearate; PEG-100 Stearate; phenoxyethanol; xanthan gum; cetostearyl alcohol; bentonite; citric acid monohydrate; sodium citrate; sodium hydroxide; edetate disodium; ethylhexylglycerin; allantoin; chamomile flower oil; panthenol

Drug Facts

Active Ingredient

Benzoyl Peroxide 2.5%

Purpose

Acne Treatment

Uses

- for the management of acne

Warnings

For external use only

Do not use if you

- Have very sensitive skin
- Are sensitive to benzoyl peroxide

Ask a doctor or pharmacist before use if you are using other topical acne medications at the same time or immediately following use of this product.

When using this product

- Avoid unnecessary sun exposure and use a sunscreen.
- Avoid contact with lips, eyes, or mouth.
- Skin irritation may occur, characterized by redness, burning, itching, peeling, or possible swelling. Irritation may be reduced by using the product less frequently or in lower concentration.
- Avoid contact with hair and dyed fabrics, which may be bleached by this product.

Stop use and ask a doctor if irritation becomes severe.

Keep out of reach of children. Do not swallow. If swallowed, get medical help or contact a Poison Control Center right away.

Directions

- Clean the skin thoroughly before applying this product.
- Start with one application daily then gradually increase to 2-3 times daily as needed.
- If going outside apply sunscreen after using this product.
- If bothersome dryness or peeling occurs, reduce application to once a day or every other day.
- Avoid storing at extreme temperatures (below 40°F and above 100°F).

Inactive ingredients

Water, Caprylic/Capric Triglyceride, Propanediol, Methyl Methacrylate/Glycol Dimethacrylate Crosspolymer, Dimethicone, Cyclopentasiloxane, Steareth-20, Cyclohexasiloxane, Glyceryl Stearate, PEG-100 Stearate, Phenoxyethanol, Xanthan Gum, Cetearyl Alcohol, Bentonite, Citric Acid, Sodium Citrate, Disodium EDTA, Ethylhexylglycerin, Sodium Hydroxide, Allantoin, Chamomilla Recutita (Matricaria) Flower Oil, Panthenol

Microsponge® is a registered trademark of AMCOL International Corp.

Save carton for complete labeling

M050735

Distributed by: CVS Pharmacy, Inc.

One CVS Drive, Woonsocket, RI 02895

© 2014 CVS/pharmacy

CVS.com® 1-800-SHOP CVS

Made in the U.S.A. of U.S. and imported components

V-31490

CVS® Quality

Money Back Guarantee

#971012

FP415

M050735

Principal Display Panel - Carton Label

SKIN+PHARMACY

ADVANCED
ACNE THERAPY

TARGETED TREATMENT WIPES
with Microsponge® Technology

2.5% Benzoyl Peroxide

- effectively kills acne-causing bacteria
- promotes healthier, clearer skin
- fragrance free

DERMATOLOGIST TESTED

exclusively at
CVS/pharmacy

2 packs/10 wipes each ● Total 20 pre-moistened wipes

3.5 x 3 in (8.9 x 7.6 cm)

Principal Display Panel - Packet label

SKIN+PHARMACY

ADVANCED
ACNE THERAPY

TARGETED TREATMENT WIPES
with Microsponge® Technology

2.5% Benzoyl Peroxide

- effectively kills acne-causing bacteria
- promotes healthier, clearer skin
- fragrance free

DERMATOLOGIST TESTED

exclusively at
CVS/pharmacy

10 pre-moistened wipes ● 3.5 x 3 in (8.9 x 7.6 cm)

M050744